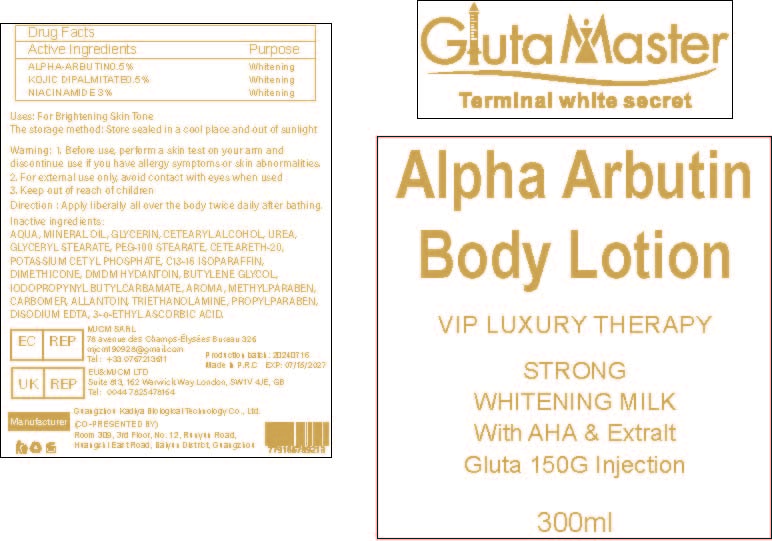 DRUG LABEL: Brightening BodyLotion
NDC: 84423-030 | Form: EMULSION
Manufacturer: Guangzhou Kadiya Biotechnology Co., Ltd.
Category: otc | Type: HUMAN OTC DRUG LABEL
Date: 20240724

ACTIVE INGREDIENTS: NIACINAMIDE 9 mg/300 mL; ALPHA-ARBUTIN 1.5 mg/300 mL; KOJIC DIPALMITATE 1.5 mg/300 mL
INACTIVE INGREDIENTS: BUTYLENE GLYCOL; IODOPROPYNYL BUTYLCARBAMATE; GLYCERIN; POTASSIUM CETYL PHOSPHATE; ALLANTOIN; WATER; MINERAL OIL; PROPYLPARABEN; DIMETHICONE; 3-O-ETHYL ASCORBIC ACID; CARBOXYPOLYMETHYLENE; C13-16 ISOPARAFFIN; METHYLPARABEN; DMDM HYDANTOIN; GLYCERYL MONOSTEARATE; UREA; CETOSTEARYL ALCOHOL; POLYOXYL 20 CETOSTEARYL ETHER; TROLAMINE; EDETATE DISODIUM; PEG-100 STEARATE

Uses：
For Skin Whitening

INACTIVE INGREDIENT

AQUA、MINERAL OIL、GLYCERIN、CETEARYL ALCOHOL、UREA、GLYCERYL STEARATE、PEG-100 STEARATE、CETEARETH-20、POTASSIUM CETYL PHOSPHATE、C13-16 ISOPARAFFIN、DIMETHICONE、DMDM HYDANTOIN、BUTYLENE GLYCOL、IODOPROPYNYL BUTYLCARBAMATE、AROMA、METHYLPARABEN、CARBOMER、ALLANTOIN、TRIETHANOLAMINE、PROPYLPARABEN、DISODIUM EDTA、3-o-ETHYL ASCORBIC ACID

Warning.
1.Before use, perform a skin test on your arm and discontinue use if you have allergy symptoms or skin abnormalities.
2、For external use only, avoid contact with eyes when used
3、Keep out of reach of children

INDICATIONS AND USAGE

Direction : Apply liberally all over the body twice daily after bathing.

KEEP OUT OF REACH OF CHILDREN SECTION

Active Ingredients
ALPHA-ARBUTIN0.5%
KOJIC DIPALMITATE0.5%
NIACINAMIDE 3%

DOSAGE AND ADMINISTRATION

Apply liberally all over the body twice daily after bathing.

Drug Facts
Active Ingredients
ALPHA-ARBUTIN0.5%
KOJIC DIPALMITATE0.5%
NIACINAMIDE 3%
Uses：
For Skin Whitening
The storage method：
Store sealed in a cool place and out of sunlight

Warning.
1.Before use, perform a skin test on your arm and discontinue use if you have allergy symptoms or skin abnormalities.
2、For external use only, avoid contact with eyes when used
3、Keep out of reach of children

Inactive ingredients：
AQUA、MINERAL OIL、GLYCERIN、CETEARYL ALCOHOL、UREA、GLYCERYL STEARATE、PEG-100 STEARATE、CETEARETH-20、POTASSIUM CETYL PHOSPHATE、C13-16 ISOPARAFFIN、DIMETHICONE、DMDM HYDANTOIN、BUTYLENE GLYCOL、IODOPROPYNYL BUTYLCARBAMATE、AROMA、METHYLPARABEN、CARBOMER、ALLANTOIN、TRIETHANOLAMINE、PROPYLPARABEN、DISODIUM EDTA、3-o-ETHYL ASCORBIC ACID